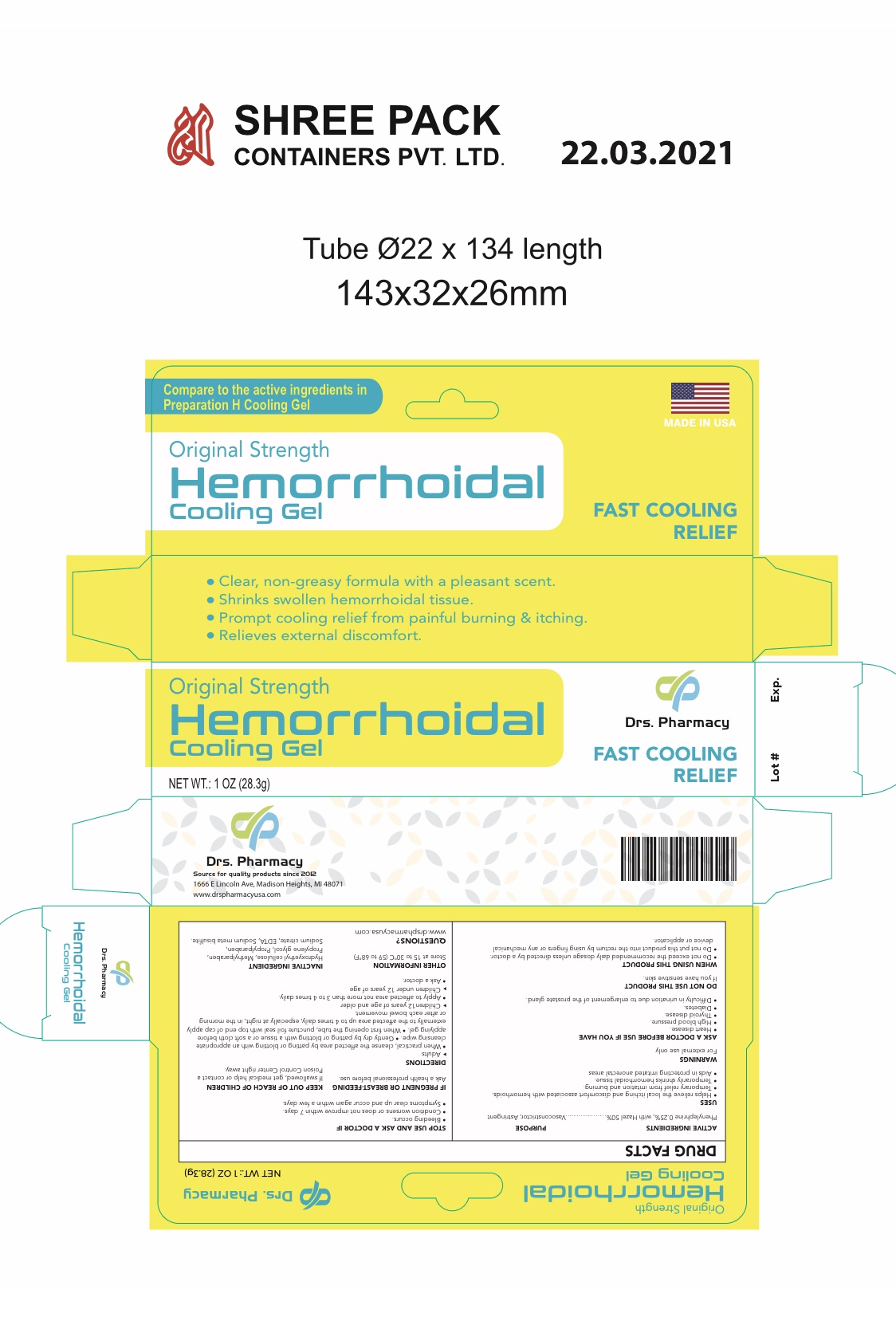 DRUG LABEL: Drs. pharmacy  HEMORRHOIDAL COOLING
NDC: 80489-959 | Form: GEL
Manufacturer: OL PHARMA TECH, LLC Drs PHARMACY
Category: otc | Type: HUMAN OTC DRUG LABEL
Date: 20250109

ACTIVE INGREDIENTS: PHENYLEPHRINE HYDROCHLORIDE 25 mg/1 g; WITCH HAZEL 500 mg/1 g
INACTIVE INGREDIENTS: PROPYLENE GLYCOL; SODIUM CITRATE, UNSPECIFIED FORM; METHYLPARABEN; EDETATE DISODIUM; PROPYLPARABEN; SODIUM METABISULFITE; HYDROXYETHYL CELLULOSE (100 MPA.S AT 2%)

ACTIVE INGREDIENT

1. Phenylephrine HCI, 0.25%
2. Witch Hazel, 50.0%

PURPOSE

- Vasoconstrictor
- Astringent

USES

- helps relieve the local itching and discomfort associated with hemorrhoids
- temporary relief of irritation and burning
- temporarily shrinks hemorrhoidal tissue
- aids in protecting irritated anorectal areas

WARNINGS

For external use only

ASK A DOCTOR BEFORE USE IF YOU HAVE

- heart disease
- high blood pressure
- thyroid disease
- diabetes
- difficulty in urination due to enlargement of the prostate gland

Ask a doctor or pharmacist before use if you are

presently taking a prescription drug for high blood pressure or depression

WHEN USING THIS PRODUCT

- do not exceed the recommended daily dosage unless directed by a doctor
- do not put this product into the rectum by using fingers or any mechanical device or applicator

STOP USING AND ASK YOUR DOCTOR IF

- bleeding occurs
- condition worsens or does not improve within 7 days

IF PREGNENT OR BREAST-FEEDING

ask a health professional before use.

KEEP OUT OF REACH OF CHILDREN

If swallowed, get medical help or contact a Poison Control Center right away.

DIRECTIONS

- adults: when practical, cleanse the affected area by patting or blotting with an appropriate cleansing wipe. Gently dry by patting or blotting with a tissue or a soft cloth before applying gel.
- when first opening the tube, puncture foil seal with top end of cap
- apply externally to the affected area up to 4 times daily, especially at night, in the morning or after each bowel movement
- children under 12 years of age: ask a doctor

OTHER INFORMATION

store at 20-25°C (68-77°F)

INACTIVE INGREDIENTS

edetate disodium, hydroxyethyl cellulose, methylparaben, propylene glycol, propylparaben, purified water, sodium citrate, sodium metabisulphite

QUESTIONS

www.drspharmacyusa.com